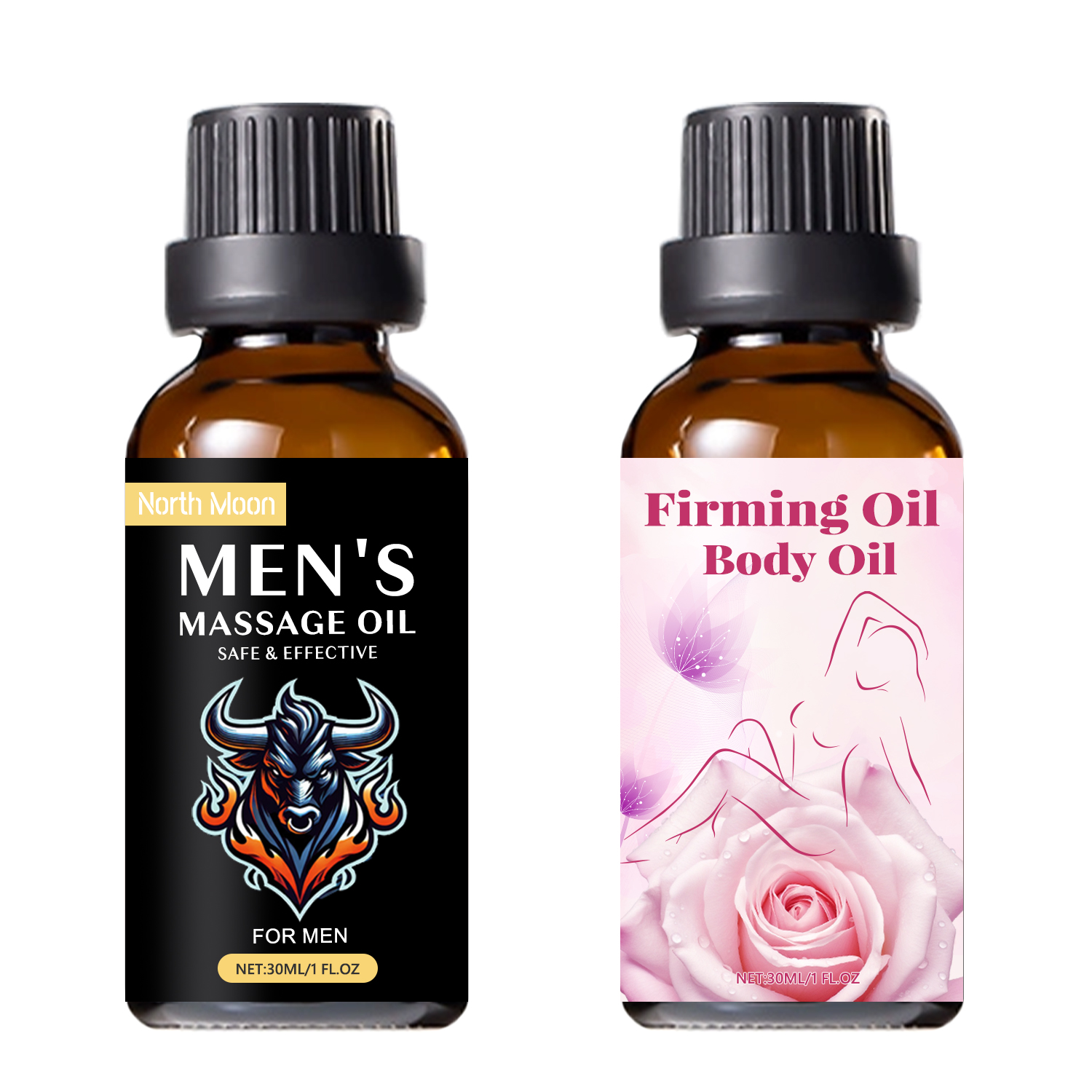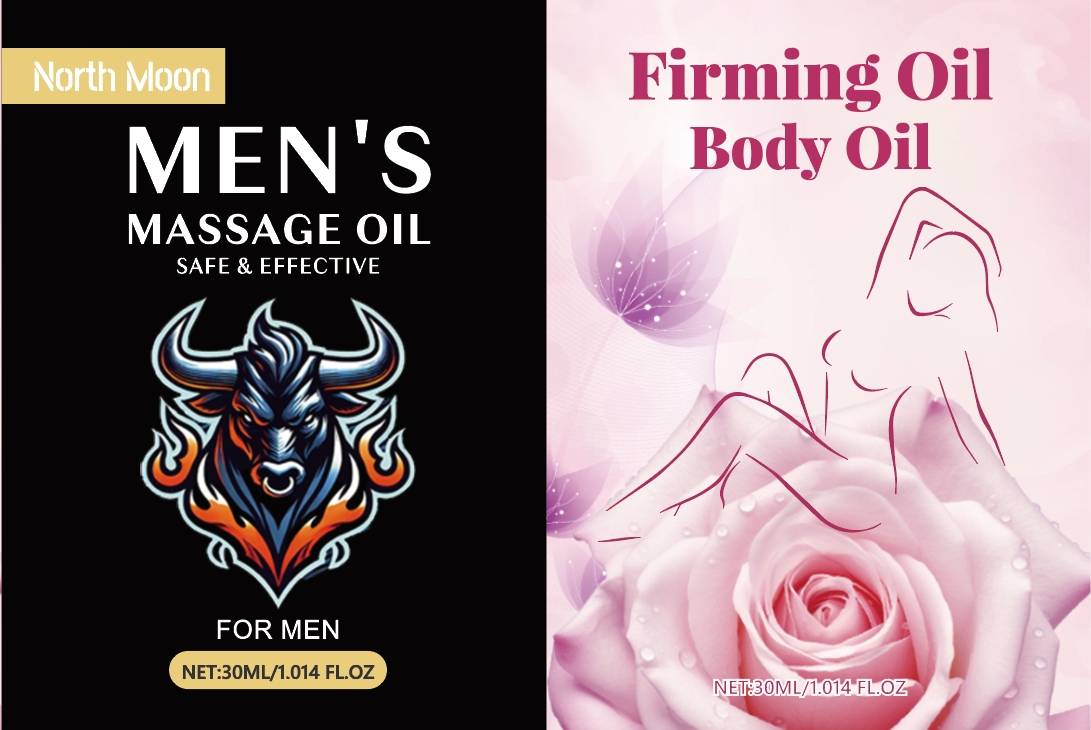 DRUG LABEL: Body Oil
NDC: 84025-215 | Form: OIL
Manufacturer: Guangzhou Yanxi Biotechnology Co., Ltd
Category: otc | Type: HUMAN OTC DRUG LABEL
Date: 20241015

ACTIVE INGREDIENTS: GLYCERIN 5 mg/100 mL; PANTHENOL 3 mg/100 mL
INACTIVE INGREDIENTS: WATER

WARNINGS

keep out of children

INACTIVE INGREDIENT

Aqua

INDICATIONS AND USAGE

Massage oil for men: Massage oils are designed specifically for men's bodies. Massage oils moisturize and soften the skin, making the skin smooth and delicate.

keep out of children

PURPOSE

This penis massage oil could promote sexual desire, gain more sexual pleasure and orgasm, delay the sexual life, and increase penis erection time.

DOSAGE AND ADMINISTRATION

Just clean the penis, apply it and gently massage to absorb